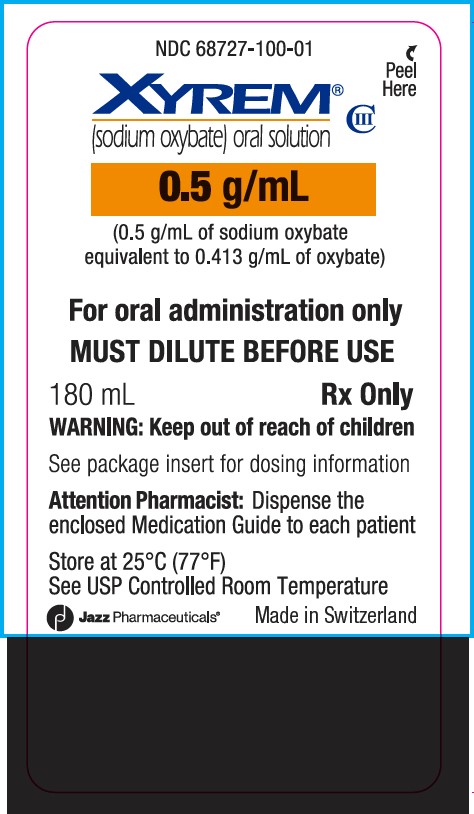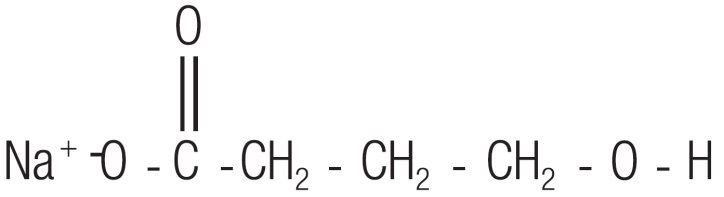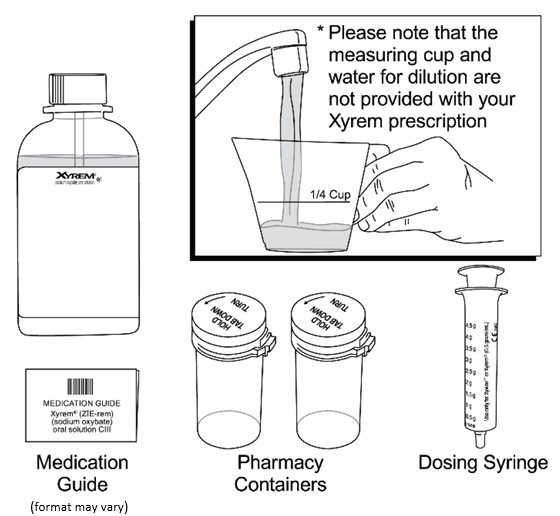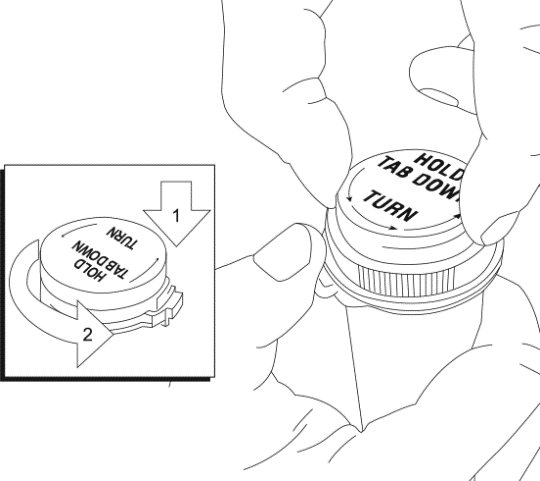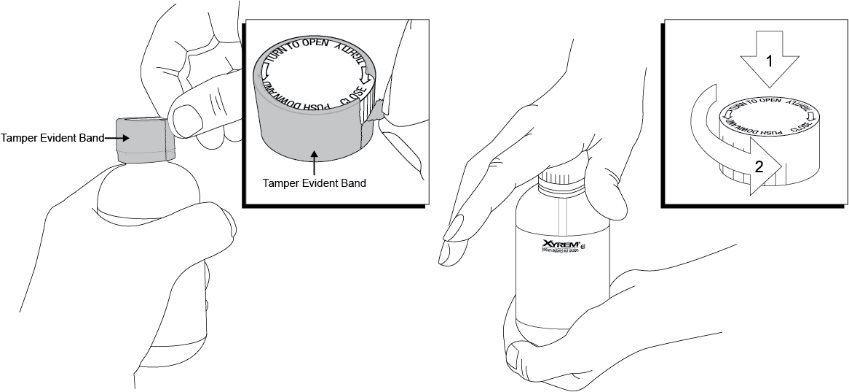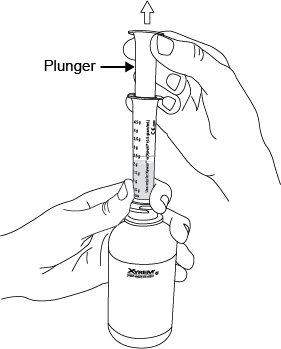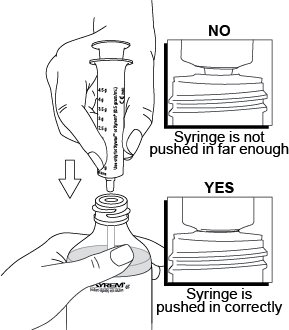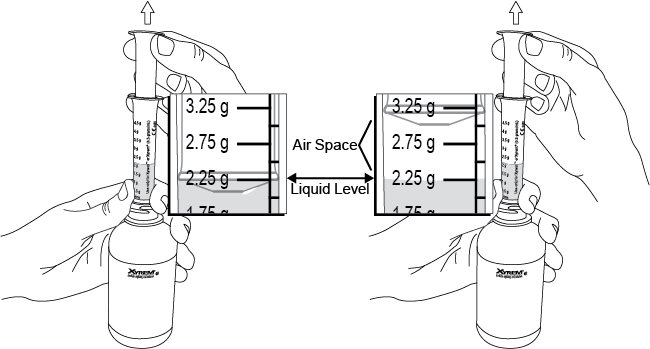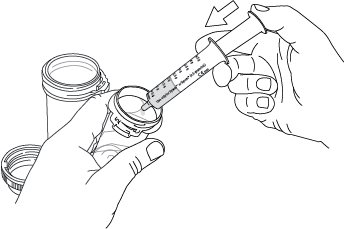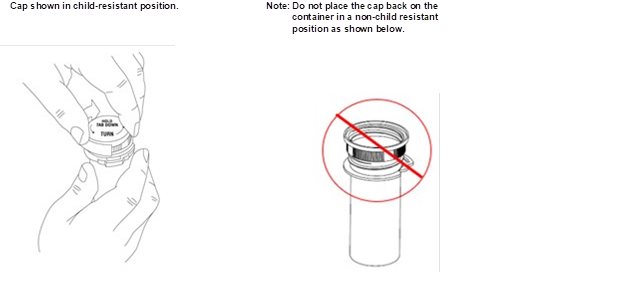 DRUG LABEL: Xyrem
NDC: 68727-100 | Form: SOLUTION
Manufacturer: Jazz Pharmaceuticals, Inc.
Category: prescription | Type: HUMAN PRESCRIPTION DRUG LABEL
Date: 20250701
DEA Schedule: CIII

ACTIVE INGREDIENTS: SODIUM OXYBATE 0.5 g/1 mL

HIGHLIGHTS OF PRESCRIBING INFORMATION

These highlights do not include all the information needed to use XYREM safely and effectively. See full prescribing information for XYREM.
XYREM® (sodium oxybate) oral solution, CIII
Initial U.S. Approval: 2002

WARNING: CENTRAL NERVOUS SYSTEM DEPRESSION and ABUSE AND MISUSE.

WARNING: CENTRAL NERVOUS SYSTEM (CNS) DEPRESSION and ABUSE AND MISUSE.

See full prescribing information for complete boxed warning.

Central Nervous System Depression

- Xyrem is a CNS depressant, and respiratory depression can occur with Xyrem use (5.1, 5.4)

Abuse and Misuse

- Xyrem is the sodium salt of gamma-hydroxybutyrate (GHB). Abuse or misuse of illicit GHB is associated with CNS adverse reactions, including seizure, respiratory depression, decreased consciousness, coma, and death (5.2, 9.2)

Xyrem is available only through a restricted program called the XYWAV and XYREM REMS (5.3)

1 INDICATIONS AND USAGE

Xyrem is a central nervous system depressant indicated for the treatment of cataplexy or excessive daytime sleepiness (EDS) in patients 7 years of age and older with narcolepsy (1).

2 DOSAGE AND ADMINISTRATION

Dosage for Adult Patients

- Initiate dosage at 4.5 g per night orally, divided into two doses (2.1).
- Titrate to effect in increments of 1.5 g per night at weekly intervals (0.75 g at bedtime and 0.75 g taken 2.5 to 4 hours later) (2.1).
- Recommended dosage range: 6 g to 9 g per night orally (2.1).

Total Nightly Dose | Take at Bedtime | Take 2.5 to 4 Hours Later
4.5 g per night | 2.25 g | 2.25 g
6 g per night | 3 g | 3 g
7.5 g per night | 3.75 g | 3.75 g
9 g per night | 4.5 g | 4.5 g

Dosage for Pediatric Patients (7 years of Age and Older)

- The recommended starting dosage, titration regimen, and maximum total nightly dosage are based on body weight (2.2).

Important Administration Information

- Prepare both doses prior to bedtime; dilute each dose with approximately ¼ cup of water in pharmacy-provided containers (2.3).
- Allow 2 hours after eating before dosing (2.3).
- Take each dose while in bed and lie down after dosing (2.3).

Patients with Hepatic Impairment

Recommended starting dosage is one-half of the original dosage per night administered orally, divided into two doses (2.4).

3 DOSAGE FORMS AND STRENGTHS

Oral solution, 0.5 g per mL (3)

4 CONTRAINDICATIONS

- In combination with sedative hypnotics or alcohol (4)
- Succinic semialdehyde dehydrogenase deficiency (4)

5 WARNINGS AND PRECAUTIONS

- CNS depression: Use caution when considering the concurrent use of Xyrem with other CNS depressants (5.1).
- Caution patients against hazardous activities requiring complete mental alertness or motor coordination within the first 6 hours of dosing or after first initiating treatment until certain that Xyrem does not affect them adversely (5.1).
- Depression and suicidality: Monitor patients for emergent or increased depression and suicidality (5.5).
- Confusion/Anxiety: Monitor for impaired motor/cognitive function (5.6).
- Parasomnias: Evaluate episodes of sleepwalking (5.7).
- High sodium content in Xyrem: Monitor patients with heart failure, hypertension, or impaired renal function (5.8).

6 ADVERSE REACTIONS

Most common adverse reactions in adults (≥5% and at least twice the incidence with placebo) were nausea, dizziness, vomiting, somnolence, enuresis, and tremor (6.1).

Most common adverse reactions in pediatric patients (≥5%) were nausea, enuresis, vomiting, headache, weight decreased, decreased appetite, dizziness, and sleepwalking (6.1).
To report SUSPECTED ADVERSE REACTIONS, contact Jazz Pharmaceuticals, Inc. at 1-800-520-5568, or FDA at 1-800-FDA-1088 or www.fda.gov/Medwatch.

7 DRUG INTERACTIONS

- Concomitant use with divalproex sodium: An initial reduction in Xyrem dose of at least 20% is recommended (2.5, 7.2).

8 USE IN SPECIFIC POPULATIONS

- Pregnancy: Based on animal data, may cause fetal harm (8.1).
- Geriatric patients: Monitor for impaired motor and/or cognitive function when taking Xyrem (8.5).

FULL PRESCRIBING INFORMATION

WARNING: CENTRAL NERVOUS SYSTEM DEPRESSION and ABUSE AND MISUSE.

- Central Nervous System Depression
  Xyrem (sodium oxybate) is a CNS depressant. In clinical trials at recommended doses, obtundation and clinically significant respiratory depression occurred in adult patients treated with Xyrem [see Warnings and Precautions (5.1)]. Many patients who received Xyrem during clinical trials in narcolepsy were receiving central nervous system stimulants [see Clinical Trials (14)].
- Abuse and Misuse
  Xyrem® (sodium oxybate) is the sodium salt of gamma-hydroxybutyrate (GHB). Abuse or misuse of illicit GHB, either alone or in combination with other CNS depressants, is associated with CNS adverse reactions, including seizure, respiratory depression, decreases in the level of consciousness, coma, and death [see Warnings and Precautions (5.2)].
  Because of the risks of CNS depression and abuse and misuse, Xyrem is available only through a restricted program under a Risk Evaluation and Mitigation Strategy (REMS) called the XYWAV and XYREM REMS [see Warnings and Precautions (5.3)].

1 INDICATIONS AND USAGE

Xyrem is indicated for the treatment of cataplexy or excessive daytime sleepiness (EDS) in patients 7 years of age and older with narcolepsy.

2 DOSAGE AND ADMINISTRATION

2.1 Adult Dosing Information

The recommended starting dosage is 4.5 grams (g) per night administered orally, divided into two doses: 2.25 g at bedtime and 2.25 g taken 2.5 to 4 hours later (see Table 1). Increase the dosage by 1.5 g per night at weekly intervals (additional 0.75 g at bedtime and 0.75 g taken 2.5 to 4 hours later) to the effective dosage range of 6 g to 9 g per night orally. The dosage may be gradually titrated based on efficacy and tolerability. Doses higher than 9 g per night have not been studied and should not ordinarily be administered.

Table 1: Recommended Adult Xyrem Dose Regimen (g = grams)

If a Patient’s Total Nightly Dose is: | Take at Bedtime: | Take 2.5 to 4 Hours Later:
4.5 g per night | 2.25 g | 2.25 g
6 g per night | 3 g | 3 g
7.5 g per night | 3.75 g | 3.75 g
9 g per night | 4.5 g | 4.5 g

2.2 Pediatric Dosing Information

Xyrem is administered orally twice nightly. The recommended starting pediatric dosage, titration regimen, and maximum total nightly dosage are based on patient weight, as specified in Table 2. The dosage may be gradually titrated based on efficacy and tolerability.

Table 2: Recommended Pediatric Xyrem Dosage for Patients 7 Years of Age and Older*

Patient Weight | Initial Dosage |  | Maximum Weekly Dosage Increase |  | Maximum Recommended Dosage
Patient Weight | Take at Bedtime: | Take 2.5 to 4 Hours Later: | Take at Bedtime: | Take 2.5 to 4 Hours Later: | Take at Bedtime: | Take 2.5 to 4 Hours Later:
<20 kg** | There is insufficient information to provide specific dosing recommendations for patients who weigh less than 20 kg.
20 kg to <30 kg | ≤1 g | ≤1 g | 0.5 g | 0.5 g | 3 g | 3 g
30 kg to <45 kg | ≤1.5 g | ≤1.5 g | 0.5 g | 0.5 g | 3.75 g | 3.75 g
≥45 kg | ≤2.25 g | ≤2.25 g | 0.75 g | 0.75 g | 4.5 g | 4.5 g

* For patients who sleep more than 8 hours per night, the first dose of Xyrem may be given at bedtime or after an initial period of sleep.

** If Xyrem is used in patients 7 years of age and older who weigh less than 20 kg, a lower starting dosage, lower maximum weekly dosage increases, and lower total maximum nightly dosage should be considered.

Note: Some patients may achieve better responses with unequal doses at bedtime and 2.5 to 4 hours later.

2.3 Important Administration Instructions for All Patients

The total nightly dosage of Xyrem is divided into two doses. Prepare both doses of Xyrem prior to bedtime. Prior to ingestion, each dose of Xyrem should be diluted with approximately ¼ cup (approximately 60 mL) of water in the empty pharmacy containers provided.

Take the first nightly dose of Xyrem at least 2 hours after eating [see Clinical Pharmacology (12.3)]. Take the second nightly dose 2.5 to 4 hours after the first dose.

Patients should take both doses of Xyrem while in bed and lie down immediately after dosing, and remain in bed following ingestion of each dose. Xyrem may cause patients to fall asleep abruptly without first feeling drowsy [see Adverse Reactions (6.2)]. Patients will often fall asleep within 5 minutes of taking Xyrem, and will usually fall asleep within 15 minutes, though the time it takes any individual patient to fall asleep may vary from night to night. Patients may need to set an alarm to awaken for the second dose. Rarely, patients may take up to 2 hours to fall asleep.

If the second dose is missed, that dose should be skipped and Xyrem should not be taken again until the next night. Both Xyrem doses should never be taken at one time.

2.4 Dosage Modification in Patients with Hepatic Impairment

The recommended starting dosage in patients with hepatic impairment is one-half of the original dosage per night, administered orally divided into two doses [see Use in Specific Populations (8.6) and Clinical Pharmacology (12.3)].

2.5 Dosage Adjustment with Co-administration of Divalproex Sodium

When initiating divalproex sodium in patients taking a stable dosage of Xyrem, a reduction of the Xyrem dosage by at least 20% is recommended with initial concomitant use [see Drug Interactions (7.2) and Clinical Pharmacology (12.3)]. When initiating Xyrem in patients already taking divalproex sodium, a lower starting dosage of Xyrem is recommended. Subsequently, the dosage of Xyrem can be adjusted based on individual clinical response and tolerability.

3 DOSAGE FORMS AND STRENGTHS

Xyrem is a clear to slightly opalescent oral solution, in a concentration of 0.5 g per mL (0.5 g/mL of sodium oxybate equivalent to 0.413 g/mL of oxybate).

4 CONTRAINDICATIONS

Xyrem is contraindicated for use in:

- combination with sedative hypnotics [see Warnings and Precautions (5.1)].
- combination with alcohol [see Warnings and Precautions (5.1)].
- patients with succinic semialdehyde dehydrogenase deficiency [see Clinical Pharmacology (12.3)].

5 WARNINGS AND PRECAUTIONS

5.1 Central Nervous System Depression

Xyrem is a central nervous system (CNS) depressant. In adult clinical trials at recommended doses, obtundation and clinically significant respiratory depression occurred in patients treated with Xyrem. Xyrem is contraindicated in combination with alcohol and sedative hypnotics. The concurrent use of Xyrem with other CNS depressants, including but not limited to opioid analgesics, benzodiazepines, sedating antidepressants or antipsychotics, sedating anti-epileptic drugs, general anesthetics, muscle relaxants, and/or illicit CNS depressants, may increase the risk of respiratory depression, hypotension, profound sedation, syncope, and death. If use of these CNS depressants in combination with Xyrem is required, dose reduction or discontinuation of one or more CNS depressants (including Xyrem) should be considered. In addition, if short-term use of an opioid (e.g., post- or perioperative) is required, interruption of treatment with Xyrem should be considered.

Healthcare providers should caution patients about operating hazardous machinery, including automobiles or airplanes, until they are reasonably certain that Xyrem does not affect them adversely (e.g., impair judgment, thinking, or motor skills). Patients should not engage in hazardous occupations or activities requiring complete mental alertness or motor coordination, such as operating machinery or a motor vehicle or flying an airplane, for at least 6 hours after taking Xyrem. Patients should be queried about CNS depression‐related events upon initiation of Xyrem therapy and periodically thereafter.

Xyrem is available only through a restricted program under a REMS [see Warnings and Precautions (5.3)].

5.2 Abuse and Misuse

Xyrem is a Schedule III controlled substance. The active ingredient of Xyrem, sodium oxybate or gamma-hydroxybutyrate (GHB), is a Schedule I controlled substance. Abuse of illicit GHB, either alone or in combination with other CNS depressants, is associated with CNS adverse reactions, including seizure, respiratory depression, decreases in the level of consciousness, coma, and death. The rapid onset of sedation, coupled with the amnestic features of Xyrem, particularly when combined with alcohol, has proven to be dangerous for the voluntary and involuntary user (e.g., assault victim). Because illicit use and abuse of GHB have been reported, physicians should carefully evaluate patients for a history of drug abuse and follow such patients closely, observing them for signs of misuse or abuse of GHB (e.g., increase in size or frequency of dosing, drug-seeking behavior, feigned cataplexy) [see Drug Abuse and Dependence (9.2)].

Xyrem is available only through a restricted program under a REMS [see Warnings and Precautions (5.3)].

5.3 XYWAV and XYREM REMS

Xyrem is available only through a restricted distribution program called the XYWAV and XYREM REMS because of the risks of central nervous system depression and abuse and misuse [see Warnings and Precautions (5.1, 5.2)].

Notable requirements of the XYWAV and XYREM REMS include the following:

- Healthcare Providers who prescribe Xyrem are specially certified
- Xyrem will be dispensed only by the central pharmacy that is specially certified
- Xyrem will be dispensed and shipped only to patients who are enrolled in the XYWAV and XYREM REMS with documentation of safe use

Further information is available at www.XYWAVXYREMREMS.com or 1-866-997-3688.

5.4 Respiratory Depression and Sleep-Disordered Breathing

Xyrem may impair respiratory drive, especially in patients with compromised respiratory function. In overdoses, life-threatening respiratory depression has been reported [see Overdosage (10)].

In an adult study assessing the respiratory-depressant effects of Xyrem at doses up to 9 g per night in 21 patients with narcolepsy, no dose-related changes in oxygen saturation were demonstrated in the group as a whole. One of the four patients with preexisting, moderate-to-severe sleep apnea had significant worsening of the apnea/hypopnea index during treatment.

In an adult study assessing the effects of Xyrem 9 g per night in 50 patients with obstructive sleep apnea, Xyrem did not increase the severity of sleep-disordered breathing and did not adversely affect the average duration and severity of oxygen desaturation overall. However, there was a significant increase in the number of central apneas in patients taking Xyrem, and clinically significant oxygen desaturation (≤55%) was measured in three patients (6%) after Xyrem administration, with one patient withdrawing from the study and two continuing after single brief instances of desaturation.

During polysomnographic evaluation (PSG), central sleep apnea and oxygen desaturation were observed in pediatric patients with narcolepsy treated with Xyrem.

Prescribers should be aware that increased central apneas and clinically relevant desaturation events have been observed with Xyrem administration in adult and pediatric patients.

In adult clinical trials in 128 patients with narcolepsy, two subjects had profound CNS depression, which resolved after supportive respiratory intervention. Two other patients discontinued sodium oxybate because of severe difficulty breathing and an increase in obstructive sleep apnea. In two controlled trials assessing PSG measures in adult patients with narcolepsy, 40 of 477 patients were included with a baseline apnea/hypopnea index of 16 to 67 events per hour, indicative of mild to severe sleep-disordered breathing. None of the 40 patients had a clinically significant worsening of respiratory function as measured by apnea/hypopnea index and pulse oximetry at doses of 4.5 g to 9 g per night.

Prescribers should be aware that sleep-related breathing disorders tend to be more prevalent in obese patients, in men, in postmenopausal women not on hormone replacement therapy and among patients with narcolepsy.

5.5 Depression and Suicidality

In adult clinical trials in patients with narcolepsy (n=781), there were two suicides and two attempted suicides in patients treated with Xyrem, including three patients with a previous history of depressive psychiatric disorder. Of the two suicides, one patient used Xyrem in conjunction with other drugs. Xyrem was not involved in the second suicide. Adverse reactions of depression were reported by 7% of 781 patients treated with Xyrem, with four patients (<1%) discontinuing because of depression. In most cases, no change in Xyrem treatment was required.

In a controlled adult trial, with patients randomized to fixed doses of 3 g, 6 g, or 9 g per night Xyrem or placebo, there was a single event of depression at the 3 g per night dose. In another adult controlled trial, with patients titrated from an initial 4.5 g per night starting dose, the incidences of depression were 1 (1.7%), 1 (1.5%), 2 (3.2%), and 2 (3.6%) for the placebo, 4.5 g, 6 g, and 9 g per night doses, respectively.

In the pediatric clinical trial in patients with narcolepsy (n=104), one patient experienced suicidal ideation and two patients reported depression while taking Xyrem.

The emergence of depression in patients treated with Xyrem requires careful and immediate evaluation. Patients with a previous history of a depressive illness and/or suicide attempt should be monitored carefully for the emergence of depressive symptoms while taking Xyrem.

5.6 Other Behavioral or Psychiatric Adverse Reactions

During adult clinical trials in patients with narcolepsy, 3% of 781 patients treated with Xyrem experienced confusion, with incidence generally increasing with dose.

Less than 1% of patients discontinued the drug because of confusion. Confusion was reported at all recommended doses from 6 g to 9 g per night. In a controlled trial in adults where patients were randomized to fixed total daily doses of 3 g, 6 g, or 9 g per night or placebo, a dose-response relationship for confusion was demonstrated, with 17% of patients at 9 g per night experiencing confusion. In all cases in that controlled trial, the confusion resolved soon after termination of treatment. In Trial 3 where sodium oxybate was titrated from an initial 4.5 g per night dose, there was a single event of confusion in one patient at the 9 g per night dose. In the majority of cases in all adult clinical trials in patients with narcolepsy, confusion resolved either soon after termination of dosing or with continued treatment.

Anxiety occurred in 5.8% of the 874 patients receiving Xyrem in adult clinical trials in another population.

Other neuropsychiatric reactions reported in adult clinical trials in patients with narcolepsy and the post-marketing setting included hallucinations, paranoia, psychosis, aggression, and agitation.

In the pediatric clinical trial in patients with narcolepsy, neuropsychiatric reactions, including acute psychosis, confusion, and anxiety, were reported while taking Xyrem.

The emergence or increase in the occurrence of behavioral or psychiatric events in adult and pediatric patients taking Xyrem should be carefully monitored.

5.7 Parasomnias

Sleepwalking, defined as confused behavior occurring at night and at times associated with wandering, was reported in 6% of 781 patients with narcolepsy treated with Xyrem in adult controlled trials and long-term open-label studies, with <1% of patients discontinuing due to sleepwalking. Rates of sleepwalking were similar for patients taking placebo and patients taking Xyrem in controlled trials. It is unclear if some or all of the reported sleepwalking episodes correspond to true somnambulism, which is a parasomnia occurring during non-REM sleep, or to any other specific medical disorder. Five instances of sleepwalking with potential injury or significant injury were reported during a clinical trial of Xyrem in patients with narcolepsy.

Parasomnias, including sleepwalking, also have been reported in the pediatric clinical trial and in postmarketing experience with Xyrem. Therefore, episodes of sleepwalking should be fully evaluated and appropriate interventions considered.

5.8 Use in Patients Sensitive to High Sodium Intake

Xyrem has a high salt content. In patients sensitive to salt intake (e.g., those with heart failure, hypertension, or renal impairment), consider the amount of daily sodium intake in each dose of Xyrem. Table 3 provides the approximate sodium content per Xyrem dose.
Table 3
Approximate Sodium Content per Total Nightly Dose of Xyrem (g = grams)

Xyrem Dose | Sodium Content/Total Nightly Exposure
3 g per night | 550 mg
4.5 g per night | 820 mg
6 g per night | 1100 mg
7.5 g per night | 1400 mg
9 g per night | 1640 mg

6 ADVERSE REACTIONS

The following clinically significant adverse reactions appear in other sections of the labeling:

- CNS depression [see Warnings and Precautions (5.1)]
- Abuse and Misuse [see Warnings and Precautions (5.2)]
- Respiratory Depression and Sleep-Disordered Breathing [see Warnings and Precautions (5.4)]
- Depression and Suicidality [see Warnings and Precautions (5.5)]
- Other Behavioral or Psychiatric Adverse Reactions [see Warnings and Precautions (5.6)]
- Parasomnias [see Warnings and Precautions (5.7)]
- Use in Patients Sensitive to High Sodium Intake [see Warnings and Precautions (5.8)]

6.1 Clinical Trials Experience

Because clinical trials are conducted under widely varying conditions, adverse reaction rates observed in the clinical trials of a drug cannot be directly compared to rates in the clinical trials of another drug and may not reflect the rates observed in clinical practice.

Adult Patients

Xyrem was studied in three placebo-controlled clinical trials (Trials N1, N3, and N4, described in Sections 14.1 and 14.2) in 611 patients with narcolepsy (398 subjects treated with Xyrem, and 213 with placebo). A total of 781 patients with narcolepsy were treated with Xyrem in controlled and uncontrolled clinical trials.

Section 6.1 and Table 4 present adverse reactions from three pooled, controlled trials (N1, N3, N4) in patients with narcolepsy.

Adverse Reactions Leading to Treatment Discontinuation:

Of the 398 patients with narcolepsy treated with Xyrem, 10.3% of patients discontinued because of adverse reactions compared with 2.8% of patients receiving placebo. The most common adverse reaction leading to discontinuation was nausea (2.8%). The majority of adverse reactions leading to discontinuation began during the first few weeks of treatment.

Commonly Observed Adverse Reactions in Controlled Clinical Trials:

The most common adverse reactions (incidence ≥5% and twice the rate seen with placebo) in patients treated with Xyrem were nausea, dizziness, vomiting, somnolence, enuresis, and tremor.

Adverse Reactions Occurring at an Incidence of 2% or Greater:

Table 4 lists adverse reactions that occurred at a frequency of 2% or more in any treatment group for three controlled trials and were more frequent in any Xyrem treatment group than with placebo. Adverse reactions are summarized by dose at onset. Nearly all patients in these studies initiated treatment at 4.5 g per night. In patients who remained on treatment, adverse reactions tended to occur early and to diminish over time.
Table 4
Adverse Reactions Occurring in ≥2% of Adult Patients and More Frequently with Xyrem than Placebo in Three Controlled Trials (N1, N3, N4) by Body System and Dose at Onset

Adverse Reaction | Placebo (n=213) % | Xyrem 4.5g (n=185) % | Xyrem 6g (n=258) % | Xyrem 9g (n=178) %
ANY ADVERSE REACTION | 62 | 45 | 55 | 70
GASTROINTESTINAL DISORDERS
Nausea | 3 | 8 | 13 | 20
Vomiting | 1 | 2 | 4 | 11
Diarrhea | 2 | 4 | 3 | 4
Abdominal pain upper | 2 | 3 | 1 | 2
Dry mouth | 2 | 1 | 2 | 1
GENERAL DISORDERS AND ADMINISTRATIVE SITE CONDITIONS
Pain | 1 | 1 | <1 | 3
Feeling drunk | 1 | 0 | <1 | 3
Edema peripheral | 1 | 3 | 0 | 0
MUSCULOSKELETAL AND CONNECTIVE TISSUE DISORDERS
Cataplexy | 1 | 1 | 1 | 2
Muscle spasms | 2 | 2 | <1 | 2
Pain in extremity | 1 | 3 | 1 | 1
NERVOUS SYSTEM DISORDERS
Dizziness | 4 | 9 | 11 | 15
Somnolence | 4 | 1 | 3 | 8
Tremor | 0 | 0 | 2 | 5
Disturbance in attention | 0 | 1 | 0 | 4
Paresthesia | 1 | 2 | 1 | 3
Sleep paralysis | 1 | 0 | 1 | 3
PSYCHIATRIC DISORDERS
Disorientation | 1 | 1 | 2 | 3
Irritability | 1 | 0 | <1 | 3
Sleepwalking | 0 | 0 | 0 | 3
Anxiety | 1 | 1 | 1 | 2
RENAL AND URINARY DISORDERS
Enuresis | 1 | 3 | 3 | 7
SKIN AND SUBCUTANEOUS TISSUE DISORDERS
Hyperhidrosis | 0 | 1 | 1 | 3

Dose-Response Information

In clinical trials in narcolepsy, a dose-response relationship was observed for nausea, vomiting, paresthesia, disorientation, irritability, disturbance in attention, feeling drunk, sleepwalking, and enuresis. The incidence of all these reactions was notably higher at 9 g per night.

In controlled trials in narcolepsy, discontinuations of treatment due to adverse reactions were greater at higher doses of Xyrem.

Pediatric Patients (7 Years of Age and Older)

In the pediatric clinical trial (Trial N5), 104 patients aged 7 to 17 years (37 patients aged 7 to 11 years; 67 patients aged 12 to 17 years) with narcolepsy received Xyrem for up to one year. This study included an open-label safety continuation period in which eligible patients received Xyrem for up to an additional 2 years. The median and maximum exposure across the entire study were 371 and 987 days, respectively.

Adverse Reactions Leading to Treatment Discontinuation

In the pediatric clinical trial, 7 of 104 patients reported adverse reactions that led to withdrawal from the study (hallucination, tactile; suicidal ideation; weight decreased; sleep apnea syndrome; affect lability; anger, anxiety, depression; and headache).

Adverse Reactions in the Pediatric Clinical Trial

The most common adverse reactions (≥5%) were nausea (20%), enuresis (19%), vomiting (18%), headache (17%), weight decreased (13%), decreased appetite (9%), dizziness (8%), and sleepwalking (6%).

Additional information regarding safety in pediatric patients appears in the following sections:

- Respiratory Depression and Sleep-Disordered Breathing [see Warnings and Precautions (5.4)]
- Depression and Suicidality [see Warnings and Precautions (5.5)]
- Other Behavioral or Psychiatric Adverse Reactions [see Warnings and Precautions (5.6)]
- Parasomnias [see Warnings and Precautions (5.7)]

The overall adverse reaction profile of Xyrem in the pediatric clinical trial was similar to that seen in the adult clinical trial program.

6.2 Postmarketing Experience

The following adverse reactions have been identified during postapproval use of Xyrem. Because these reactions are reported voluntarily from a population of uncertain size, it is not always possible to reliably estimate their frequency or establish a causal relationship to drug exposure:

arthralgia, decreased appetite, fall*, fluid retention, hangover, headache, hypersensitivity, hypertension, memory impairment, nocturia, panic attack, vision blurred, and weight decreased.
* The sudden onset of sleep in patients taking sodium oxybate, including in a standing position or while rising from bed, has led to falls complicated by injuries, in some cases requiring hospitalization.

7 DRUG INTERACTIONS

7.1 Alcohol, Sedative Hypnotics, and CNS Depressants

Xyrem is contraindicated for use in combination with alcohol or sedative hypnotics. Use of other CNS depressants may potentiate the CNS-depressant effects of Xyrem [see Warnings and Precautions (5.1)].

7.2 Divalproex Sodium

Concomitant use of Xyrem with divalproex sodium results in an increase in systemic exposure to GHB, which was shown to cause a greater impairment on some tests of attention and working memory in a clinical study [see Clinical Pharmacology (12.3)]. An initial dose reduction of Xyrem is recommended when used concomitantly with divalproex sodium [see Dosage and Administration (2.5)]. Prescribers are advised to monitor patient response closely and adjust dose accordingly if concomitant use of Xyrem and divalproex sodium is warranted.

8 USE IN SPECIFIC POPULATIONS

8.1 Pregnancy

Risk Summary

There are no adequate data on the developmental risk associated with the use of sodium oxybate in pregnant women. Oral administration of sodium oxybate to pregnant rats (150, 350, or 1,000 mg/kg/day) or rabbits (300, 600, or 1,200 mg/kg/day) throughout organogenesis produced no clear evidence of developmental toxicity; however, oral administration to rats throughout pregnancy and lactation resulted in increased stillbirths and decreased offspring postnatal viability and growth, at a clinically relevant dose [see Data].

In the U.S. general population, the estimated background risk of major birth defects and miscarriage in clinically recognized pregnancies is 2-4% and 15-20%, respectively. The background risk of major birth defects and miscarriage for the indicated population is unknown.

Clinical Considerations

Labor or Delivery

Xyrem has not been studied in labor or delivery. In obstetric anesthesia using an injectable formulation of sodium oxybate, newborns had stable cardiovascular and respiratory measures but were very sleepy, causing a slight decrease in Apgar scores. There was a fall in the rate of uterine contractions 20 minutes after injection. Placental transfer is rapid and gamma-hydroxybutyrate (GHB) has been detected in newborns at delivery after intravenous administration of GHB to mothers. Subsequent effects of sodium oxybate on later growth, development, and maturation in humans are unknown.

Data

Animal Data

Oral administration of sodium oxybate to pregnant rats (150, 350, or 1,000 mg/kg/day) or rabbits (300, 600, or 1,200 mg/kg/day) throughout organogenesis produced no clear evidence of developmental toxicity. The highest doses tested in rats and rabbits were approximately 1 and 3 times, respectively, the maximum recommended human dose (MRHD) of 9 g per night on a body surface area (mg/m^2) basis.

Oral administration of sodium oxybate (150, 350, or 1,000 mg/kg/day) to rats throughout pregnancy and lactation resulted in increased stillbirths and decreased offspring postnatal viability and body weight gain at the highest dose tested. The no-effect dose for pre- and post-natal developmental toxicity in rats is less than the MRHD on a mg/m^2 basis.

8.2 Lactation

Risk Summary

GHB is excreted in human milk after oral administration of sodium oxybate. There is insufficient information on the risk to a breastfed infant, and there is insufficient information on milk production in nursing mothers. The developmental and health benefits of breastfeeding should be considered along with the mother's clinical need for Xyrem and any potential adverse effects on the breastfed infant from Xyrem or from the underlying maternal condition.

8.4 Pediatric Use

The safety and effectiveness of Xyrem in the treatment of cataplexy or excessive daytime sleepiness in pediatric patients (7 years of age and older) with narcolepsy have been established in a double-blind, placebo-controlled, randomized-withdrawal study [see Adverse Reactions (6.1) and Clinical Studies (14.3)].

In the pediatric clinical trial with Xyrem administration in patients with narcolepsy, serious adverse reactions of central sleep apnea and oxygen desaturation documented by polysomnography evaluation; depression; suicidal ideation; neuropsychiatric reactions including acute psychosis, confusion, and anxiety; and parasomnias, including sleepwalking, have been reported [see Warnings and Precautions (5.4, 5.5, 5.6, 5.7) and Adverse Reactions (6.1)].

Safety and effectiveness of Xyrem in pediatric patients below the age of 7 years have not been established.

Juvenile Animal Toxicity Data

In a study in which sodium oxybate (0, 100, 300, or 900 mg/kg/day) was orally administered to rats during the juvenile period of development (postnatal days 21 through 90), mortality was observed at the two highest doses tested. Deaths occurred during the first week of dosing and were associated with clinical signs (including decreased activity and respiratory rate) consistent with the pharmacological effects of the drug. Reduced body weight gain in males and females and delayed sexual maturation in males were observed at the highest dose tested. The no-effect dose for adverse effects in juvenile rats is associated with plasma exposures (AUC) less than that at the maximum recommended human dose (9 g/night).

8.5 Geriatric Use

Clinical studies of Xyrem in patients with narcolepsy did not include sufficient numbers of subjects age 65 years and older to determine whether they respond differently from younger subjects. In controlled trials in another population, 39 (5%) of 874 patients were 65 years or older. Discontinuations of treatment due to adverse reactions were increased in the elderly compared to younger adults (21% vs. 19%). Frequency of headaches was markedly increased in the elderly (39% vs. 19%). The most common adverse reactions were similar in both age categories. In general, dose selection for an elderly patient should be cautious, usually starting at the low end of the dosing range, reflecting the greater frequency of decreased hepatic, renal, or cardiac function, and of concomitant disease or other drug therapy.

8.6 Hepatic Impairment

Because of an increase in exposure to Xyrem, the starting dose should be reduced by half in patients with hepatic impairment [see Dosage and Administration (2.4) and Clinical Pharmacology (12.3)].

9 DRUG ABUSE AND DEPENDENCE

9.1 Controlled Substance

Xyrem is a Schedule III controlled substance under the Federal Controlled Substances Act. Non-medical use of Xyrem could lead to penalties assessed under the higher Schedule I controls.

9.2 Abuse

Xyrem (sodium oxybate), the sodium salt of GHB, produces dose-dependent central nervous system effects, including hypnotic and positive subjective reinforcing effects. The onset of effect is rapid, enhancing its potential for abuse or misuse.

Drug abuse is the intentional non-therapeutic use of a drug product or substance, even once, for its desirable psychological or physiological effects. Misuse is the intentional use, for therapeutic purposes of a drug by an individual in a way other than prescribed by a health care provider or for whom it was not prescribed. Drug misuse and abuse may occur with or without progression to addiction. Drug addiction is a cluster of behavioral, cognitive, and physiological phenomena that may include a strong desire to take the drug, difficulties in controlling drug use (e.g., continuing drug use despite harmful consequences, giving a higher priority to drug use than other activities and obligations), and possible tolerance or physical dependence.

The rapid onset of sedation, coupled with the amnestic features of GHB, particularly when combined with alcohol, has proven to be dangerous for the voluntary and involuntary user (e.g., assault victim).

Illicit GHB is abused in social settings primarily by young adults. Some of the doses estimated to be abused are in a similar dosage range to that used for treatment of patients with cataplexy. GHB has some commonalities with ethanol over a limited dose range, and some cross tolerance with ethanol has been reported as well. Cases of severe dependence and craving for GHB have been reported when the drug is taken around the clock. Patterns of abuse indicative of dependence include: 1) the use of increasingly large doses, 2) increased frequency of use, and 3) continued use despite adverse consequences.

Because illicit use and abuse of GHB have been reported, physicians should carefully evaluate patients for a history of drug abuse and follow such patients closely, observing them for signs of misuse or abuse of GHB (e.g., increase in size or frequency of dosing, drug-seeking behavior, feigned cataplexy). Dispose of Xyrem according to state and federal regulations. It is safe to dispose of Xyrem down the sanitary sewer.

9.3 Dependence

Physical dependence is a state that develops as a result of physiological adaptation in response to repeated drug use, manifested by withdrawal signs and symptoms after abrupt discontinuation or a significant dose reduction of a drug. There have been case reports of withdrawal, ranging from mild to severe, following discontinuation of illicit use of GHB at frequent repeated doses (18 g to 250 g per day) in excess of the recommended dosage range. Signs and symptoms of GHB withdrawal following abrupt discontinuation included insomnia, restlessness, anxiety, psychosis, lethargy, nausea, tremor, sweating, muscle cramps, tachycardia, headache, dizziness, rebound fatigue and sleepiness, confusion, and, particularly in the case of severe withdrawal, visual hallucinations, agitation, and delirium. These symptoms generally abated in 3 to 14 days. In cases of severe withdrawal, hospitalization may be required. The discontinuation effects of Xyrem have not been systematically evaluated in controlled clinical trials. In the clinical trial experience with Xyrem in narcolepsy/cataplexy patients at recommended doses, two patients reported anxiety and one reported insomnia following abrupt discontinuation at the termination of the clinical trial; in the two patients with anxiety, the frequency of cataplexy had increased markedly at the same time.

Tolerance

Tolerance is a physiological state characterized by a reduced response to a drug after repeated administration (i.e., a higher dose of a drug is required to produce the same effect that was once obtained at a lower dose). Tolerance to Xyrem has not been systematically studied in controlled clinical trials. There have been some case reports of symptoms of tolerance developing after illicit use at dosages far in excess of the recommended Xyrem dosage regimen. Clinical studies of sodium oxybate in the treatment of alcohol withdrawal suggest a potential cross-tolerance with alcohol. The safety and effectiveness of Xyrem in the treatment of alcohol withdrawal have not been established.

10 OVERDOSAGE

10.1 Human Experience

Information regarding overdose with Xyrem is derived largely from reports in the medical literature that describe symptoms and signs in individuals who have ingested GHB illicitly. In these circumstances the co-ingestion of other drugs and alcohol was common, and may have influenced the presentation and severity of clinical manifestations of overdose.

In adult clinical trials two cases of overdose with Xyrem were reported. In the first case, an estimated dose of 150 g, more than 15 times the maximum recommended dose, caused a patient to be unresponsive with brief periods of apnea and to be incontinent of urine and feces. This individual recovered without sequelae. In the second case, death was reported following a multiple drug overdose consisting of Xyrem and numerous other drugs.

10.2 Signs and Symptoms

Information about signs and symptoms associated with overdosage with Xyrem derives from reports of illicit use of GHB. Patient presentation following overdose is influenced by the dose ingested, the time since ingestion, the co-ingestion of other drugs and alcohol, and the fed or fasted state. Patients have exhibited varying degrees of depressed consciousness that may fluctuate rapidly between a confusional, agitated combative state with ataxia and coma. Emesis (even when obtunded), diaphoresis, headache, and impaired psychomotor skills have been observed. No typical pupillary changes have been described to assist in diagnosis; pupillary reactivity to light is maintained. Blurred vision has been reported. An increasing depth of coma and acidosis have been observed at higher doses. Myoclonus and tonic-clonic seizures have been reported. Respiration may be unaffected or compromised in rate and depth. Cheyne-Stokes respiration and apnea have been observed. Bradycardia and hypothermia may accompany unconsciousness, as well as muscular hypotonia, but tendon reflexes remain intact.

10.3 Recommended Treatment of Overdose

General symptomatic and supportive care should be instituted immediately, and gastric decontamination may be considered if co-ingestants are suspected. Because emesis may occur in the presence of obtundation, appropriate posture (left lateral recumbent position) and protection of the airway by intubation may be warranted. Although the gag reflex may be absent in deeply comatose patients, even unconscious patients may become combative to intubation, and rapid-sequence induction (without the use of sedative) should be considered. Vital signs and consciousness should be closely monitored. The bradycardia reported with GHB overdose has been responsive to atropine intravenous administration. No reversal of the central depressant effects of Xyrem can be expected from naloxone or flumazenil administration. The use of hemodialysis and other forms of extracorporeal drug removal have not been studied in GHB overdose, but have been reported in cases of acidosis associated with GHB ingestions of 125 g or greater; however, due to the rapid metabolism of sodium oxybate, these measures may not be warranted.

10.4 Poison Control Center

As with the management of all cases of drug overdosage, the possibility of multiple drug ingestion should be considered. The healthcare provider is encouraged to collect urine and blood samples for routine toxicologic screening, and to consult with a regional poison control center (1-800-222-1222) for current treatment recommendations.

11 DESCRIPTION

Sodium oxybate, a CNS depressant, is the active ingredient in Xyrem. The chemical name for sodium oxybate is sodium 4-hydroxybutyrate. The molecular formula is C4H7NaO3, and the molecular weight is 126.09 g/mole. The chemical structure is:

Sodium oxybate is a white to off-white, crystalline powder that is very soluble in aqueous solutions. Each mL of Xyrem contains 0.5 g of sodium oxybate (equivalent to 0.413 g/mL of oxybate) in USP Purified Water, neutralized to pH 7.5 with malic acid.

12 CLINICAL PHARMACOLOGY

12.1 Mechanism of Action

Xyrem is a CNS depressant. The mechanism of action of Xyrem in the treatment of narcolepsy is unknown. Sodium oxybate is the sodium salt of gamma-hydroxybutyrate (GHB), an endogenous compound and metabolite of the neurotransmitter GABA. It is hypothesized that the therapeutic effects of Xyrem on cataplexy and excessive daytime sleepiness are mediated through GABAB actions at noradrenergic and dopaminergic neurons, as well as at thalamocortical neurons.

12.3 Pharmacokinetics

Pharmacokinetics of GHB are nonlinear and are similar following single or repeat dosing of Xyrem.

Absorption

Following oral administration of Xyrem, GHB is absorbed rapidly across the clinical dose range, with an absolute bioavailability of about 88%. The average peak plasma concentrations (Cmax) following administration of each of the two 2.25 g doses given under fasting conditions 4 hours apart were similar. The average time to peak plasma concentration (Tmax) ranged from 0.5 to 1.25 hours. Following oral administration of Xyrem, the plasma levels of GHB increased more than dose-proportionally, with blood levels increasing 3.7‐fold as total daily dose is doubled from 4.5 g to 9 g. Single doses greater than 4.5 g have not been studied.

Effect of Food

Administration of Xyrem immediately after a high-fat meal resulted in delayed absorption (average Tmax increased from 0.75 hr to 2 hr) and a reduction in Cmax of GHB by a mean of 59% and of systemic exposure (AUC) by 37%.

Distribution

GHB is a hydrophilic compound with an apparent volume of distribution averaging 190 mL/kg to 384 mL/kg. At GHB concentrations ranging from 3 mcg/mL to 300 mcg/mL, less than 1% is bound to plasma proteins.

Elimination

Metabolism

Animal studies indicate that metabolism is the major elimination pathway for GHB, producing carbon dioxide and water via the tricarboxylic acid (Krebs) cycle and secondarily by beta-oxidation. The primary pathway involves a cytosolic NADP^+-linked enzyme, GHB dehydrogenase, that catalyzes the conversion of GHB to succinic semialdehyde, which is then biotransformed to succinic acid by the enzyme succinic semialdehyde dehydrogenase. Succinic acid enters the Krebs cycle where it is metabolized to carbon dioxide and water. A second mitochondrial oxidoreductase enzyme, a transhydrogenase, also catalyzes the conversion to succinic semialdehyde in the presence of α-ketoglutarate. An alternate pathway of biotransformation involves β-oxidation via 3,4-dihydroxybutyrate to carbon dioxide and water. No active metabolites have been identified.

Excretion

The clearance of GHB is almost entirely by biotransformation to carbon dioxide, which is then eliminated by expiration. On average, less than 5% of unchanged drug appears in human urine within 6 to 8 hours after dosing. Fecal excretion is negligible. GHB has an elimination half-life of 0.5 to 1 hour.

Specific Populations

Geriatric Patients

There is limited experience with Xyrem in the elderly. Results from a pharmacokinetic study (n=20) in another studied population indicate that the pharmacokinetic characteristics of GHB are consistent among younger (age 48 to 64 years) and older (age 65 to 75 years) adults.

Pediatric Patients

The pharmacokinetics of sodium oxybate were evaluated in pediatric patients from 7 to 17 years of age (n=29). The pharmacokinetic characteristics of sodium oxybate were shown to be similar in adults and pediatric patients. Body weight was found to be the major intrinsic factor affecting oxybate pharmacokinetics.

Male and Female Patients

In a study of 18 female and 18 male healthy adult volunteers, no gender differences were detected in the pharmacokinetics of GHB following a single Xyrem oral dose of 4.5 g.

Racial or Ethnic Groups

There are insufficient data to evaluate any pharmacokinetic differences among races.

Patients with Renal Impairment

No pharmacokinetic study in patients with renal impairment has been conducted.

Patients with Hepatic Impairment

The pharmacokinetics of GHB in 16 cirrhotic patients, half without ascites (Child’s Class A) and half with ascites (Child’s Class C), were compared to the kinetics in 8 subjects with normal hepatic function after a single Xyrem oral dose of 25 mg/kg. AUC values were double in the cirrhotic patients, with apparent oral clearance reduced from 9.1 mL/min/kg in healthy adults to 4.5 and 4.1 mL/min/kg in Class A and Class C patients, respectively. Elimination half-life was significantly longer in Class C and Class A patients than in control patients (mean t1/2 of 59 and 32 minutes, respectively, versus 22 minutes). The starting dose of Xyrem should be reduced in patients with liver impairment [see Dosage and Administration (2.4) and Use in Specific Populations (8.6)].

Drug Interactions Studies

Studies in vitro with pooled human liver microsomes indicate that sodium oxybate does not significantly inhibit the activities of the human isoenzymes CYP1A2, CYP2C9, CYP2C19, CYP2D6, CYP2E1, or CYP3A up to the concentration of 3 mM (378 mcg/mL), a level considerably higher than levels achieved with recommended doses.

Drug interaction studies in healthy adults (age 18 to 50 years) were conducted with Xyrem and divalproex sodium, diclofenac, and ibuprofen:

- Divalproex sodium: Co-administration of Xyrem (6 g per day as two equal doses of 3 grams dosed four hours apart) with divalproex sodium (valproic acid, 1250 mg per day) increased mean systemic exposure to GHB as shown by AUC by approximately 25% (AUC ratio range of 0.8 to 1.7), while Cmax was comparable. Co-administration did not appear to affect the pharmacokinetics of valproic acid. A greater impairment on some tests of attention and working memory was observed with co-administration of both drugs than with either drug alone [see Drug Interactions (7.2) and Dosage and Administration (2.5)].
- Diclofenac: Co-administration of Xyrem (6 g per day as two equal doses of 3 grams dosed four hours apart) with diclofenac (50 mg/dose twice per day) showed no significant differences in systemic exposure to GHB. Co-administration did not appear to affect the pharmacokinetics of diclofenac.
- Ibuprofen: Co-administration of Xyrem (6 g per day as two equal doses of 3 grams dosed four hours apart) with ibuprofen (800 mg/dose four times per day also dosed four hours apart) resulted in comparable systemic exposure to GHB as shown by plasma Cmax and AUC values. Co-administration did not affect the pharmacokinetics of ibuprofen.

Drug interaction studies in healthy adults demonstrated no pharmacokinetic interactions between Xyrem and protriptyline hydrochloride, zolpidem tartrate, and modafinil. Also, there were no pharmacokinetic interactions with the alcohol dehydrogenase inhibitor fomepizole. However, pharmacodynamic interactions with these drugs cannot be ruled out. Alteration of gastric pH with omeprazole produced no significant change in the pharmacokinetics of GHB. In addition, drug interaction studies in healthy adults demonstrated no pharmacokinetic or clinically significant pharmacodynamic interactions between Xyrem and duloxetine HCl.

13 NONCLINICAL TOXICOLOGY

13.1 Carcinogenesis, Mutagenesis, Impairment of Fertility

Carcinogenesis

Administration of sodium oxybate to rats at oral doses of up to 1,000 mg/kg/day for 83 (males) or 104 (females) weeks resulted in no increase in tumors. Plasma exposure (AUC) at the highest dose tested was 2 times that in humans at the maximum recommended human dose (MRHD) of 9 g per night.

The results of 2-year carcinogenicity studies in mouse and rat with gamma-butyrolactone, a compound that is metabolized to sodium oxybate in vivo, showed no clear evidence of carcinogenic activity. The plasma AUCs of sodium oxybate achieved at the highest doses tested in these studies were less than that in humans at the MRHD.

Mutagenesis

Sodium oxybate was negative in the in vitro bacterial gene mutation assay, an in vitro chromosomal aberration assay in mammalian cells, and in an in vivo rat micronucleus assay.

Impairment of Fertility

Oral administration of sodium oxybate (150, 350, or 1,000 mg/kg/day) to male and female rats prior to and throughout mating and continuing in females through early gestation resulted in no adverse effects on fertility. The highest dose tested is approximately equal to the MRHD on a mg/m^2 basis.

14 CLINICAL STUDIES

The efficacy of Xyrem for the treatment of cataplexy or excessive daytime sleepiness (EDS) in patients 7 years of age and older with narcolepsy has been established in the following adequate and well-controlled trials:

- Cataplexy in adult narcolepsy in Trials N1 and N2 [see Clinical Studies (14.1)]
- Excessive Daytime Sleepiness (EDS) in adult narcolepsy in Trials N3 and N4 [see Clinical Studies (14.2)]
- Cataplexy and EDS in pediatric narcolepsy in Trial N5 [see Clinical Studies (14.3)]

14.1 Cataplexy in Adult Narcolepsy

The effectiveness of Xyrem in the treatment of cataplexy was established in two randomized, double-blind, placebo-controlled, multicenter, parallel-group trials (Trials N1 and N2) in patients with narcolepsy (see Table 5). In Trials N1 and N2, 85% and 80% of patients, respectively, were also being treated with CNS stimulants. The high percentages of concomitant stimulant use make it impossible to assess the efficacy and safety of Xyrem independent of stimulant use. In each trial, the treatment period was 4 weeks and the total nightly Xyrem doses ranged from 3 g to 9 g, with the total nightly dose administered as two equal doses. The first dose each night was taken at bedtime and the second dose was taken 2.5 to 4 hours later. There were no restrictions on the time between food consumption and dosing.

Trial N1 enrolled 136 narcoleptic patients with moderate to severe cataplexy (median of 21 cataplexy attacks per week) at baseline. Prior to randomization, medications with possible effects on cataplexy were withdrawn, but stimulants were continued at stable doses. Patients were randomized to receive placebo, Xyrem 3 g per night, Xyrem 6 g per night, or Xyrem 9 g per night.

Trial N2 was a randomized-withdrawal trial with 55 narcoleptic patients who had been taking open-label Xyrem for 7 to 44 months prior to study entry. To be included, patients were required to have a history of at least 5 cataplexy attacks per week prior to any treatment for cataplexy. Patients were randomized to continued treatment with Xyrem at their stable dose (ranging from 3 g to 9 g per night) or to placebo for 2 weeks. Trial N2 was designed specifically to evaluate the continued efficacy of sodium oxybate after long-term use.

The primary efficacy measure in Trials N1 and N2 was the frequency of cataplexy attacks.

Table 5
Median Number of Cataplexy Attacks in Trials N1 and N2

Trial/Dosage Group | Baseline | Median Change from Baseline | Comparison to Placebo (p-value)
Trial N1 (Prospective, Randomized, Parallel Group Trial)
 |  | (median attacks/week)
Placebo (n=33) | 20.5 | -4 | –
Xyrem 6 g per night (n=31) | 23.0 | -10 | 0.0451
Xyrem 9 g per night (n=33) | 23.5 | -16 | 0.0016
Trial N2 (Randomized-Withdrawal Trial)
 |  | (median attacks/2 weeks)
Placebo (n=29) | 4.0 | 21 | –
Xyrem (n=26) | 1.9 | 0 | <0.001

In Trial N1, both the 6 g and 9 g per night Xyrem doses resulted in statistically significant reductions in the frequency of cataplexy attacks. The 3 g per night dose had little effect. In Trial N2, patients randomized to placebo after discontinuing long-term open-label Xyrem therapy experienced a significant increase in cataplexy attacks (p<0.001), providing evidence of long-term efficacy of Xyrem. In Trial N2, the response was numerically similar for patients treated with doses of 6 g to 9 g per night, but there was no effect seen in patients treated with doses less than 6 g per night, suggesting little effect at these doses.

14.2 Excessive Daytime Sleepiness in Adult Narcolepsy

The effectiveness of Xyrem in the treatment of excessive daytime sleepiness in patients with narcolepsy was established in two randomized, double-blind, placebo-controlled trials (Trials N3 and N4) (see Tables 6 to 8). Seventy-eight percent of patients in Trial N3 were also being treated with CNS stimulants.

Trial N3 was a multicenter randomized, double-blind, placebo-controlled, parallel-group trial that evaluated 228 patients with moderate to severe symptoms at entry into the study including a median Epworth Sleepiness Scale (see below) score of 18, and a Maintenance of Wakefulness Test (see below) score of 8.3 minutes. Patients were randomized to one of 4 treatment groups: placebo, Xyrem 4.5 g per night, Xyrem 6 g per night, or Xyrem 9 g per night. The period of double-blind treatment in this trial was 8 weeks. Antidepressants were withdrawn prior to randomization; stimulants were continued at stable doses.

The primary efficacy measures in Trial N3 were the Epworth Sleepiness Scale and the Clinical Global Impression of Change. The Epworth Sleepiness Scale is intended to evaluate the extent of sleepiness in everyday situations by asking the patient a series of questions. In these questions, patients were asked to rate their chances of dozing during each of 8 activities on a scale from 0-3 (0=never; 1=slight; 2=moderate; 3=high). Higher total scores indicate a greater tendency to sleepiness. The Clinical Global Impression of Change is evaluated on a 7-point scale, centered at No Change, and ranging from Very Much Worse to Very Much Improved. In Trial N3, patients were rated by evaluators who based their assessments on the severity of narcolepsy at baseline.

In Trial N3, statistically significant improvements were seen on the Epworth Sleepiness Scale score at Week 8 and on the Clinical Global Impression of Change score at Week 8 with the 6 g and 9 g per night doses of Xyrem compared to the placebo group.

Table 6
Change from Baseline in Daytime Sleepiness Score (Epworth Sleepiness Scale) at Week 8 in Trial N3 (Range 0-24)

Treatment Group | Baseline | Week 8 | Median Change from Baseline at Week 8 | p-value
Placebo (n=59) | 17.5 | 17.0 | -0.5 | -
Xyrem 6 g per night (n=58) | 19.0 | 16.0 | -2.0 | <0.001
Xyrem 9 g per night (n=47) | 19.0 | 12.0 | -5.0 | <0.001

Table 7
Proportion of Patients with a Very Much or Much Improved Clinical Global Impression of Change in Daytime and Nighttime Symptoms in Trial N3

Treatment Group | Percentages of Responders (Very Much Improved or Much Improved) | Change from Baseline; Significance Compared to Placebo (p-value)
Placebo (n=59) | 22% | -
Xyrem 6 g per night (n=58) | 52% | <0.001
Xyrem 9 g per night (n=47) | 64% | <0.001

Trial N4 was a multicenter randomized, double-blind, placebo-controlled, parallel-group trial that evaluated 222 patients with moderate to severe symptoms at entry into the study including a median Epworth Sleepiness Scale score of 15, and a Maintenance of Wakefulness Test (see below) score of 10.3 minutes. At entry, patients had to be taking modafinil at stable doses of 200 mg, 400 mg, or 600 mg daily for at least 1 month prior to randomization. The patients enrolled in the study were randomized to one of 4 treatment groups: placebo, Xyrem, modafinil, or Xyrem plus modafinil. Xyrem was administered in a dose of 6 g per night for 4 weeks, followed by 9 g per night for 4 weeks. Modafinil was continued in the modafinil alone and the Xyrem plus modafinil treatment groups at the patient’s prior dose. Trial N4 was not designed to compare the effects of Xyrem to modafinil because patients receiving modafinil were not titrated to a maximal dose. Patients randomized to placebo or to Xyrem treatment were withdrawn from their stable dose of modafinil. Patients taking antidepressants could continue these medications at stable doses.

The primary efficacy measure in Trial N4 was the Maintenance of Wakefulness Test. The Maintenance of Wakefulness Test measures latency to sleep onset (in minutes) averaged over 4 sessions at 2-hour intervals following nocturnal polysomnography. For each test session, the subject was asked to remain awake without using extraordinary measures. Each test session is terminated after 20 minutes if no sleep occurs, or after 10 minutes, if sleep occurs. The overall score is the mean sleep latency for the 4 sessions.

In Trial N4, a statistically significant improvement in the change in the Maintenance of Wakefulness Test score from baseline at Week 8 was seen in the Xyrem and Xyrem plus modafinil groups compared to the placebo group.

This trial was not designed to compare the effects of Xyrem to modafinil, because patients receiving modafinil were not titrated to a maximally effective dose.

Table 8
Change in Baseline in the Maintenance of Wakefulness Test Score (in minutes) at Week 8 in Trial N4

Treatment Group | Baseline | Week 8 | Mean Change from Baseline at Week 8 | p-value
Placebo (modafinil withdrawn) (n=55) | 9.7 | 6.9 | -2.7 | -
Xyrem (modafinil withdrawn) (n=50) | 11.3 | 12.0 | 0.6 | <0.001
Xyrem plus modafinil (n=54) | 10.4 | 13.2 | 2.7 | <0.001

14.3 Cataplexy and Excessive Daytime Sleepiness in Pediatric Narcolepsy

The effectiveness of Xyrem in the treatment of cataplexy and excessive daytime sleepiness in pediatric patients 7 years of age and older with narcolepsy was established in a double-blind, placebo-controlled, randomized-withdrawal study (Trial N5) (NCT02221869). The study was conducted in 106 pediatric patients (median age: 12 years; range: 7 to 17 years) with a baseline history of at least 14 cataplexy attacks in a typical 2-week period prior to any treatment for narcolepsy symptoms. Of the 106 patients, 2 did not receive study drug and 63 patients were randomized 1:1 either to continued treatment with Xyrem or to placebo. Randomization to placebo was stopped early as the efficacy criterion was met at the pre-planned interim analysis.

Patients entered the study either taking a stable dose of Xyrem or were Xyrem-naïve. CNS stimulants were allowed at entry, and approximately 50% of patients used a stable dose of stimulant throughout the stable-dose and double-blind periods. Xyrem-naïve patients were initiated and titrated based on body weight over a period of up to 10 weeks. The total nightly dose was administered in two divided doses, with the first dose given at nighttime and the second given 2.5 to 4 hours later [see Dosage and Administration (2.2)]. Once a stable dose of Xyrem had been achieved, these patients entered the 2-week stable-dose period; patients taking a stable dose of Xyrem at study entry remained taking this dose for 3 weeks, prior to randomization. Efficacy was established at doses ranging from 3 g to 9 g of Xyrem per night.

The primary efficacy measure was the change in frequency of cataplexy attacks. In addition, change in cataplexy severity was evaluated with the Clinical Global Impression of Change for cataplexy severity [see Clinical Studies (14.2) for description of scale]. The efficacy of Xyrem in the treatment of excessive daytime sleepiness in pediatric patients with narcolepsy was evaluated with the change in the Epworth Sleepiness Scale (Child and Adolescent) score. The Epworth Sleepiness Scale (Child and Adolescent) is a modified version of the scale used in adult clinical trials described above [see Clinical Studies (14.2) for description and scoring]. The overall change in narcolepsy condition was assessed by the Clinical Global Impression of Change for narcolepsy overall. Efficacy was assessed during or at the end of the 2-week double-blind treatment period, relative to the last 2 weeks or end of the stable-dose period (see Tables 9 and 10).

Pediatric patients taking stable doses of Xyrem who were withdrawn from Xyrem treatment and randomized to placebo during the double-blind treatment period experienced a statistically significant increase in weekly cataplexy attacks compared with patients who were randomized to continue treatment with Xyrem. Patients randomized to receive placebo during the double-blind treatment period experienced a statistically significant worsening of EDS compared with patients randomized to continue receiving Xyrem (see Table 9).

Table 9
Number of Weekly Cataplexy Attacks and Epworth Sleepiness Scale (Child and Adolescent) Score (Trial N5)

Treatment Group | Baseline*,† | Double-blind Treatment Period‡,§ | Median Change from Baseline | Comparison to Placebo (p-value¶)
Median Number of Cataplexy Attacks (attacks/week)
Placebo (n=32) | 4.7 | 21.3 | 12.7 | -
Xyrem (n=31) | 3.5 | 3.8 | 0.3 | <0.0001
Median Epworth Sleepiness Scale (Child and Adolescent) Score
Placebo (n=31**) | 11 | 12 | 3 | -
Xyrem (n=30**) | 8 | 9 | 0 | 0.0004

* For weekly number of cataplexy attacks, baseline value is calculated from the last 14 days of the stable-dose period.
† For Epworth Sleepiness Scale score, baseline value is collected at the end of stable-dose period.
‡ Weekly number of cataplexy attacks is calculated from all days within the double-blind treatment period.
§ For Epworth Sleepiness Scale, value is collected at the end of the double-blind treatment period.
¶ P-value from rank-based analysis of covariance (ANCOVA) with treatment as a factor and rank baseline value as a covariate.
** One patient in each of the treatment groups did not have baseline ESS score available and were not included in this analysis.

Patients randomized to receive placebo during the double-blind treatment period experienced a statistically significant worsening of cataplexy severity and narcolepsy overall according to the clinician’s assessment compared with patients randomized to continue receiving Xyrem (see Table 10).

Table 10
Clinical Global Impression of Change (CGIc) for Cataplexy Severity and Narcolepsy Overall (Trial N5)

Worsened, %† | CGIc Cataplexy Severity* |  | CGIc Narcolepsy Overall*
Worsened, %† | Placebo (n=32) | Xyrem (n=29) ‡ | Placebo (n=32) | Xyrem (n=29) ‡
Much worse or very much worse | 66% | 17% | 59% | 10%
p-value§ | 0.0001 |  | <0.0001

* Responses indicate change of severity or symptoms relative to receiving Xyrem treatment at baseline.
† Percentages based on total number of observed values.
‡ Two patients randomized to Xyrem did not have the CGIc assessments completed and were excluded from the analysis.
§ P-value from Pearson’s chi-square test.

16 HOW SUPPLIED/STORAGE AND HANDLING

16.1 How Supplied

Xyrem is a clear to slightly opalescent oral solution. Each prescription includes one bottle of Xyrem with attached press in bottle adaptor, an oral measuring device (plastic syringe), and a Medication Guide. The pharmacy provides two empty containers with child-resistant caps with each Xyrem shipment.

Each amber bottle contains Xyrem oral solution at a concentration of 0.5 g per mL (0.5 g/mL of sodium oxybate equivalent to 0.413 g/mL of oxybate) and has a child-resistant cap.

One 180 mL bottle NDC 68727-100-01

16.2 Storage

Keep out of reach of children.
Xyrem should be stored at 25°C (77°F); excursions permitted to 15°C to 30°C (59°F to 86°F) (see USP Controlled Room Temperature).
Dispense in tight containers.
Solutions prepared following dilution should be consumed within 24 hours.

16.3 Handling and Disposal

Xyrem is a Schedule III drug under the Controlled Substances Act. Xyrem should be handled according to state and federal regulations. It is safe to dispose of Xyrem down the sanitary sewer.

17 PATIENT COUNSELING INFORMATION

Advise the patient and/or caregiver to read the FDA-approved patient labeling (Medication Guide and Instructions for Use).

Central Nervous System Depression

Inform patients and/or caregivers that Xyrem can cause central nervous system depression, including respiratory depression, hypotension, profound sedation, syncope, and death. Instruct patients to not engage in activities requiring mental alertness or motor coordination, including operating hazardous machinery, for at least 6 hours after taking Xyrem. Instruct patients and/or their caregivers to inform their healthcare providers of all the medications they take [see Warnings and Precautions (5.1)].

Abuse and Misuse

Inform patients and/or caregivers that the active ingredient of Xyrem is gamma-hydroxybutyrate (GHB), which is associated with serious adverse reactions with illicit use and abuse [see Warnings and Precautions (5.2)].

XYWAV and XYREM REMS

Xyrem is available only through a restricted program called the XYWAV and XYREM REMS [see Warnings and Precautions (5.3)]. Inform the patient and/or caregiver of the following notable requirements:

- Xyrem is dispensed only by the central pharmacy
- Xyrem will be dispensed and shipped only to patients enrolled in the XYWAV and XYREM REMS

Xyrem is available only from the central pharmacy participating in the program. Therefore, provide patients and/or caregivers with the telephone number and website for information on how to obtain the product.

Alcohol or Sedative Hypnotics

Advise patients and/or caregivers that alcohol and other sedative hypnotics should not be taken with Xyrem [see Contraindications (4)].

Sedation

Inform patients and/or caregivers that the patient is likely to fall asleep quickly after taking Xyrem (often within 5 and usually within 15 minutes), but the time it takes to fall asleep can vary from night to night. The sudden onset of sleep, including in a standing position or while rising from bed, has led to falls complicated by injuries, in some cases requiring hospitalization [see Adverse Reactions (6.2)]. Instruct patients and/or caregivers that the patient should remain in bed following ingestion of the first and second nightly doses. Instruct patients and/or caregivers that the patient should not take their second nightly dose until 2.5 to 4 hours after the first dose [see Dosage and Administration (2.3)].

Food Effects on Xyrem

Inform patients and/or caregivers that the first nightly dose should be taken at least 2 hours after eating.

Respiratory Depression and Sleep-Disordered Breathing

Inform patients that Xyrem may impair respiratory drive, especially in patients with compromised respiratory function, and may cause apnea [see Warnings and Precautions (5.4)].

Depression and Suicidality

Instruct patients and/or caregivers to contact a healthcare provider immediately if the patient develops depressed mood, markedly diminished interest or pleasure in usual activities, significant change in weight and/or appetite, psychomotor agitation or retardation, increased fatigue, feelings of guilt or worthlessness, slowed thinking or impaired concentration, or suicidal ideation [see Warnings and Precautions (5.5)].

Other Behavioral or Psychiatric Adverse Reactions

Inform patients and/or caregivers that Xyrem can cause behavioral or psychiatric adverse reactions, including confusion, anxiety, and psychosis. Instruct them to notify their healthcare provider if any of these types of symptoms occur [see Warnings and Precautions (5.6)].

Sleepwalking

Instruct patients and/or caregivers that Xyrem has been associated with sleepwalking and other behaviors during sleep, and to contact their healthcare provider if this occurs [see Warnings and Precautions (5.7)].

Sodium Intake

Instruct patients and/or caregivers that Xyrem contains a significant amount of sodium and patients who are sensitive to sodium intake (e.g., those with heart failure, hypertension, or renal impairment) should limit their sodium intake [see Warnings and Precautions (5.8)].
Distributed By:
Jazz Pharmaceuticals, Inc.
Palo Alto, CA 94306
Protected by U.S. Patent Nos. 8,772,306; 9,050,302; 9,486,426; 10,213,400; 10,864,181; and 11,253,494.

MEDICATION GUIDE
XYREM® (ZĪE-rem)
(sodium oxybate)
oral solution, CIII

Read this Medication Guide carefully before you start or your child starts taking XYREM and each time you get or your child gets a refill. There may be new information. This information does not take the place of talking to your doctor about your or your child’s medical condition or treatment.

What is the most important information I should know about XYREM?

- XYREM is a central nervous system (CNS) depressant. Taking XYREM with other CNS depressants such as medicines used to make you or your child fall asleep, including opioid analgesics, benzodiazepines, sedating antidepressants, antipsychotics, sedating anti-epileptic medicines, general anesthetics, muscle relaxants, alcohol, or street drugs, may cause serious medical problems, including:
  - trouble breathing (respiratory depression)
  - low blood pressure (hypotension)
  - changes in alertness (drowsiness)
  - fainting (syncope)
  - death

Ask your doctor if you are not sure if you are, or your child is, taking a medicine listed above.

- XYREM is a federal controlled substance (CIII). The active ingredient of XYREM is a form of gamma-hydroxybutyrate (GHB) that is also a federal controlled substance (CI). Abuse of illegal GHB, either alone or with other CNS depressants may cause serious medical problems, including:
  - seizure
  - trouble breathing (respiratory depression)
  - changes in alertness (drowsiness)
  - coma
  - death

Call your doctor right away if you have or your child has any of these serious side effects.

- Anyone who takes XYREM should not do anything that requires them to be fully awake or is dangerous, including driving a car, using heavy machinery, or flying an airplane, for at least 6 hours after taking XYREM. Those activities should not be done until you know how XYREM affects you or your child.
- Keep XYREM in a safe place to prevent abuse and misuse. Selling or giving away XYREM may harm others, and is against the law. Tell your doctor if you have ever abused or been dependent on alcohol, prescription medicines, or street drugs.
- Because of the risk of CNS depression, abuse, and misuse, XYREM is available only by prescription, and filled through the central pharmacy in the XYWAV and XYREM REMS. You or your child must be enrolled in the XYWAV and XYREM REMS to receive XYREM. For information on how to receive XYREM visit www.XYWAVXYREMREMS.COM. Before you receive or your child receives XYREM, your doctor or pharmacist will make sure that you understand how to take XYREM safely and effectively. If you have any questions about XYREM, ask your doctor or call the XYWAV and XYREM REMS at 1-866-997-3688.

What is XYREM?

XYREM is a prescription medicine used to treat the following symptoms in people 7 years of age or older with narcolepsy:

- sudden onset of weak or paralyzed muscles (cataplexy), or
- excessive daytime sleepiness (EDS)

It is not known if XYREM is safe and effective in children less than 7 years of age.

Do not take XYREM if you or your child:

- takes other sleep medicines or sedatives (medicines that cause sleepiness)
- drinks alcohol
- has a rare problem called succinic semialdehyde dehydrogenase deficiency

Before taking XYREM, tell your doctor about all medical conditions, including if you or your child:

- have a history of drug abuse.
- have short periods of not breathing while sleeping (sleep apnea)
- has trouble breathing or has lung problems. You or your child may have a higher chance of having serious breathing problems when taking XYREM.
- have or had depression or has tried to harm yourself or themselves. You or your child should be watched carefully for new symptoms of depression.
- has or had behavior or other psychiatric problems such as:
  - anxiety
  - feeling more suspicious (paranoia)
  - acting aggressive
  - seeing or hearing things that are not real (hallucinations)
  - being out of touch with reality (psychosis)
  - agitation
- have liver problems
- are on a salt-restricted diet. XYREM contains a lot of sodium (salt) and may not be right for you or your child.
- have high blood pressure
- have heart failure
- have kidney problems
- are pregnant or plan to become pregnant. It is not known if XYREM can harm your unborn baby.
- are breastfeeding or plan to breastfeed. XYREM passes into breast milk. You and your doctor should decide if you or your child will take XYREM or breastfeed.

Tell your doctor about all the medicines you take or your child takes, including prescription and over-the-counter medicines, vitamins, and herbal supplements.

Especially, tell your doctor if you take or your child takes other medicines to help you or your child sleep (sedatives). Know the medicines you take or your child takes. Keep a list of them to show your doctor and pharmacist when you get or your child gets a new medicine.

How should I take or give XYREM?

- Read the Instructions for Use at the end of this Medication Guide for detailed instructions on how to take XYREM.
- Take or give XYREM exactly as your doctor tells you to take or give it.
- XYREM can cause physical dependence and craving for the medicine when it is not taken as directed.
- Never change the XYREM dose without talking to your doctor.
- XYREM can cause sleep very quickly without feeling drowsy. Some people fall asleep within 5 minutes and most fall asleep within 15 minutes. The time it takes to fall asleep might be different from night to night.
- Falling asleep quickly, including while standing or while getting up from the bed, has led to falls with injuries that have required some people to be hospitalized.
- XYREM is taken at night divided into 2 doses.
  - Adults: Take the first XYREM dose at bedtime while you are in bed and lie down immediately. Take the second XYREM dose 2½ to 4 hours after the first XYREM dose. You may want to set an alarm clock to make sure you wake up to take the second XYREM dose. You should remain in bed after taking the first and second doses of XYREM.
  - Children: Give the first XYREM dose at bedtime or after an initial period of sleep, while your child is in bed and have them lie down immediately. Give the second XYREM dose 2½ to 4 hours after the first XYREM dose. You may want to set an alarm clock to make sure you wake up to give the second XYREM dose. Your child should remain in bed after taking the first and second doses of XYREM.
- If you miss or your child misses the second XYREM dose, skip that dose and do not take or give XYREM again until the next night. Never take or give 2 XYREM doses at 1 time.
- Wait at least 2 hours after eating before taking XYREM.
- If you take or your child takes too much XYREM, call your doctor or go to the nearest hospital emergency room right away.

What are the possible side effects of XYREM?

XYREM can cause serious side effects, including:

- See “What is the most important information I should know about XYREM?”
- breathing problems, including:
  - slower breathing
  - trouble breathing
  - short periods of not breathing while sleeping (sleep apnea). People who already have breathing or lung problems have a higher chance of having breathing problems when they take XYREM.
- mental health problems, including:
  - confusion
  - seeing or hearing things that are not real (hallucinations)
  - unusual or disturbing thoughts (abnormal thinking)
  - feeling anxious or upset
  - depression
  - thoughts of killing yourself or trying to kill yourself
  - increased tiredness
  - feelings of guilt or worthlessness
  - difficulty concentrating

Call your doctor right away if you have or your child has symptoms of mental health problems, or a change in weight or appetite.

- sleepwalking. Sleepwalking can cause injuries. Call your doctor if you start or your child starts sleepwalking. Your doctor should check you or your child.

The most common side effects of XYREM in adults include:

- nausea
- sleepiness
- dizziness
- vomiting
- bedwetting
- tremor

The most common side effects of XYREM in children include:

- nausea
- bedwetting
- vomiting
- headache
- weight decreased
- decreased appetite
- dizziness
- sleepwalking

Side effects may increase when taking higher doses of XYREM.

These are not all the possible side effects of XYREM. For more information, ask your doctor or pharmacist. Call your doctor for medical advice about side effects. You may report side effects to FDA at 1-800-FDA-1088.

How should I store XYREM?

- Store XYREM in the original bottle prior to mixing with water. After mixing with water, store XYREM in pharmacy containers with child-resistant caps provided by the pharmacy.
- Store XYREM at room temperature between 68°F to 77°F (20°C to 25°C).
- XYREM solution prepared after mixing with water should be taken within 24 hours.
- When you have finished using a XYREM bottle:
  - empty any unused XYREM down the sink drain
  - cross out the label on the XYREM bottle with a marker
  - place the empty XYREM bottle in the trash

XYREM comes in a child-resistant package. Keep XYREM and all medicines out of the reach of children and pets.

General information about the safe and effective use of XYREM.

Medicines are sometimes prescribed for purposes other than those listed in a Medication Guide. Do not use XYREM for a condition for which it was not prescribed. Do not give XYREM to other people, even if they have the same symptoms. It may harm them.

You can ask your pharmacist or doctor for information about XYREM that is written for health professionals.

What are the ingredients in XYREM?
Active ingredients: sodium oxybate
Inactive ingredients: purified water and malic acid

Distributed By:
Jazz Pharmaceuticals, Inc.
Palo Alto, CA 94306

For more information, go to www.XYWAVXYREMREMS.com or call the XYWAV and XYREM REMS at 1-866-997-3688.

This Medication Guide has been approved by the U.S. Food and Drug Administration Revised: 7/2025

Instructions for Use
XYREM® (ZĪE-rem)
(sodium oxybate)
oral solution, CIII

Read this Instructions for Use carefully before you (or your child) start taking XYREM and each time you (or your child) get a refill. There may be new information. This information does not take the place of talking to your doctor about your (or your child’s) medical condition or treatment.

Important Information:

- You will need to split your (or your child’s) prescribed XYREM dose into 2 separate pharmacy containers for mixing.
- You will need to mix XYREM with water before you take or give your child the dose.
- Safely store the prepared XYREM doses and take within 24 hours after mixing. If the prepared dose was not taken within this time, throw the mixture away. See “Throwing away (disposing of) XYREM” section below for instructions about how to safely throw away XYREM.
- Both XYREM doses should be taken while in bed.
- The pharmacy containers may be rinsed out with water and emptied into the sink drain.

Supplies you will need for mixing and taking (or giving your child) XYREM. See Figure A:

- Bottle of XYREM medicine
- Dosing syringe for measuring and dispensing the XYREM dose
- Measuring cup that is able to measure about ¼ cup of water (not provided with the XYREM shipment)
- 2 empty pharmacy containers with child-resistant caps for mixing, storing, and taking the XYREM doses
- Alarm clock (not pictured which may be included in the first shipment)
- Medication Guide

Figure A

Step 1: Setup

- Take the XYREM bottle, syringe, and pharmacy containers out of the shipping box.
- Take the syringe out of the plastic wrapper. Use only the syringe provided with the XYREM prescription.
- Fill a measuring cup (not provided) with about ¼ cup of water available for mixing your dose.
- Make sure the pharmacy containers are empty.
- Open both pharmacy containers by holding the tab under the cap and turning counterclockwise (to the left). See Figure B.

Figure B

Remove the tamper evident band by pulling at the perforations and then remove the bottle cap from the XYREM bottle by pushing down while turning the cap counterclockwise. See Figure C.

Figure C

Step 2. Prepare the first XYREM dose (prepare before bedtime)

Place the XYREM bottle on a hard, flat surface and grip the bottle with one hand and firmly press the syringe into the center opening of the bottle with the other hand. See Figure D.

Figure D

Pull back on the plunger until the medicine flows into the syringe and the liquid level is lined up with the marking on the syringe that matches you or your child’s dose. See Figure E.

Figure E

Note: The XYREM medicine will not flow into the syringe unless you keep the bottle upright.

Figure F shows an example of drawing up a XYREM dose of 2.25 g. Figure G shows an example if an air space forms when drawing up the dose.

Figure F Figure G

Note: If an air space forms between the plunger and the liquid when drawing up the medicine, line up the liquid level with the marking on the syringe that matches your or your child’s dose. See Figure G above.

- After you draw up the first divided XYREM dose, remove the syringe from the opening of the XYREM bottle.
- Empty all of the medicine from the syringe into one of the provided empty pharmacy containers by pushing down on the plunger until it stops. See Figure H.

Figure H

- Using a measuring cup, pour about ¼ cup of water into the pharmacy container. Be careful to add only water to the pharmacy container and not more XYREM.
- All shipped bottles of XYREM contain the concentrated medicine. Water for mixing the medicine is not provided in the shipment.
- After mixing the medicine and water in the provided pharmacy container, place the child-resistant cap on the filled pharmacy container and turn the cap clockwise (to the right) until it clicks and locks into its child-resistant position. See Figure I.
- Caution: the pharmacy container cap is reversible with a non-child resistant side. See Figure J. Make sure the child-resistant side of the cap is used to prevent access to the medicine by children.

Figure I Figure J

Step 3. Prepare the second XYREM dose (prepare before bedtime)

- Repeat Step 2 drawing up the amount of medicine prescribed for your (or your child’s) second dose:
  - emptying the syringe into the second pharmacy container
  - adding about ¼ cup of water and
  - closing the pharmacy container

Step 4. Store the prepared XYREM doses

- Put the cap back on the XYREM bottle and store the XYREM bottle and both prepared doses in a safe and secure place. Store in a locked place if needed.
- Keep the XYREM bottle and both prepared XYREM doses out of the reach of children and pets.
- Rinse the syringe out with water and squirt the liquid into the sink drain by pushing down on the plunger until it stops.

Step 5. Take or give the first XYREM dose

- At bedtime, and before you take (or give) the first XYREM dose, put the second XYREM dose in a safe place. Caregivers should make sure all XYREM doses are kept in a safe place until given. You may want to set an alarm clock for 2½ to 4 hours later to make sure you wake up to take (or give) the second dose.
- When it is time to take (or give) the first XYREM dose, remove the cap from the pharmacy container by pressing down on the child-resistant locking tab and turning the cap counterclockwise.
- Drink (or have your child drink) all of the first XYREM dose while sitting in bed. Put the cap back on the first pharmacy container and immediately lie down to sleep (or have your child lie down to sleep).
- You (or your child) should fall asleep soon. Some people fall asleep within 5 minutes and most fall asleep within 15 minutes. Some patients take less time to fall asleep, and some take more time. The time it takes you (or your child) to fall asleep might be different from night to night.

Step 6. Take or give the second XYREM dose

- When you wake up 2½ to 4 hours later for your (or your child’s) second dose of XYREM, take the cap off the second pharmacy container.
- If you (or your child) wake up before the alarm and it has been at least 2½ hours since the first XYREM dose, turn off the alarm and take (or give your child) the second XYREM dose.
- Drink (or have your child drink) all of the second XYREM dose while sitting in bed. Put the cap back on the second pharmacy container and immediately lie down (or have your child lie down) to continue sleeping.

How should I store XYREM?

- Store XYREM in the original bottle prior to mixing with water. After mixing, store XYREM in the pharmacy containers provided by the pharmacy. The cap on the original bottle is child-resistant. The pharmacy container cap is child-resistant only when the child-resistant side of the cap is used.
- Store XYREM at room temperature between 68°F to 77°F (20°C to 25°C).
- XYREM solution prepared after mixing with water should be taken within 24 hours or emptied down the sink drain.

Throwing away (disposing of) XYREM

- When you have finished using a XYREM bottle:
  - empty any unused XYREM down the sink drain
  - cross out the label on the XYREM bottle with a marker (not provided with the XYREM shipment)
  - place the empty XYREM bottle in the trash
- Keep XYREM and all medicines out of the reach of children and pets.

Distributed By:
Jazz Pharmaceuticals, Inc.
Palo Alto, CA 94306

This Instructions for Use has been approved by the U.S. Food and Drug Administration. Revised: 7/2025